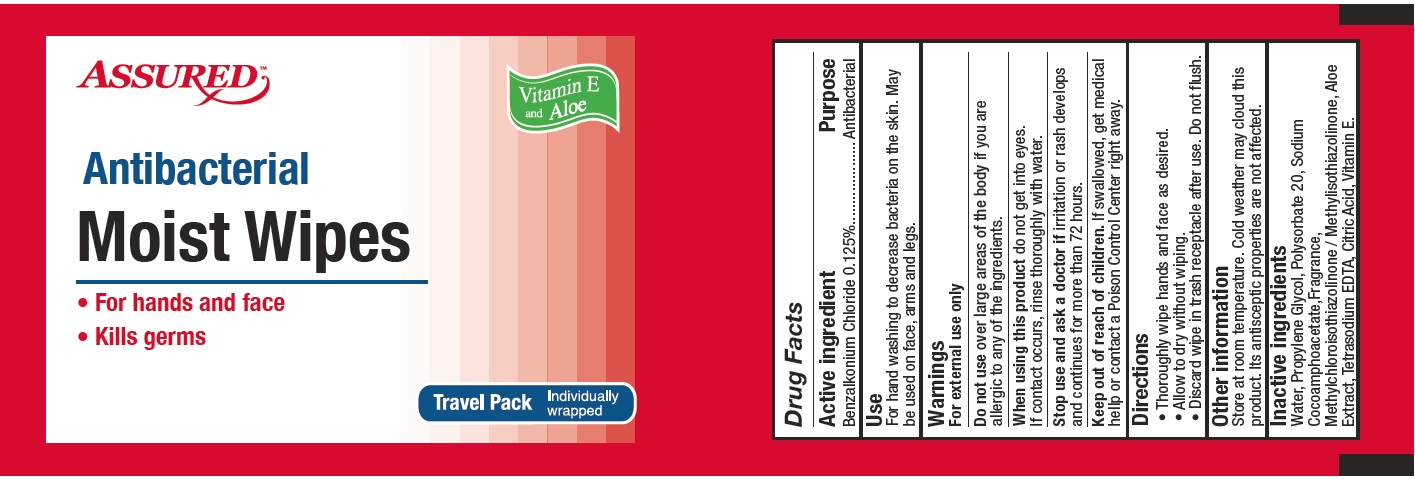 DRUG LABEL: ASSURED
NDC: 52629-800 | Form: SWAB
Manufacturer: HIGIENE + SALUD, S.A. DE C.V.
Category: otc | Type: HUMAN OTC DRUG LABEL
Date: 20220113

ACTIVE INGREDIENTS: BENZALKONIUM CHLORIDE 0.125 mg/100 mg
INACTIVE INGREDIENTS: WATER 98.54 mg/100 mg; ALOE VERA LEAF 0.05 mg/100 mg; POLYSORBATE 20 0.3 mg/100 mg; .ALPHA.-TOCOPHEROL ACETATE, DL- 0.01 mg/100 mg; PROPYLENE GLYCOL 0.5 mg/100 mg; SODIUM COCOAMPHOACETATE 0.2 mg/100 mg; METHYLCHLOROISOTHIAZOLINONE 0.1 mg/100 mg; EDETATE SODIUM 0.03 mg/100 mg; CITRIC ACID MONOHYDRATE 0.018 mg/100 mg

ACTIVE INGREDIENT

Benzalkonium Chloride 0.125%

PURPOSE

Antibacterial

WARNINGS

For external use only

DO NOT USE

Over large areas of the body if you are allergic to any of the ingredients.

WHEN USING

Do not get into eyes.

If contact occurs, rinse thoroughly with water.

STOP USE

If irritation or rash develops and continues for more than 72 hours.

ASK DOCTOR

If irritation or rash develops and continues for more than 72 hours.

KEEP OUT OF REACH OF CHILDREN

If swallowed, get medical help or contact a Poison Control Center right away.

INDICATIONS AND USAGE

· Thoroughly wipe hands and face as desired.

· allow to dry without wiping.

· Discard wipe in trash receptacle after use. Do not flush.

STORAGE AND HANDLING

Store at room temperature. Cold weather may cloud this product. It's antiseptic properties are not affected.

INACTIVE INGREDIENT

Water, Propylene Glycol, Polysorbate 20, Sodium Cocoamphoacetate, Fragrance, Methylchloroisothiazolinone/ Methylisothiazolinone, Aloe Extract, Tetrasodium EDTA, Citric Acid, Vitamin E.

Dosage: Swab - Administration: Topical

SUMMARY OF SAFETY AND EFFECTIVENESS

- Convenient

Easy to use & carry anywhere!

- Clean-up

Use to wash up quickly when soap and water are not available.

- Moisturize

Contains soothing Aloe to help moisturize your skin and leave it feeling soft and smooth.